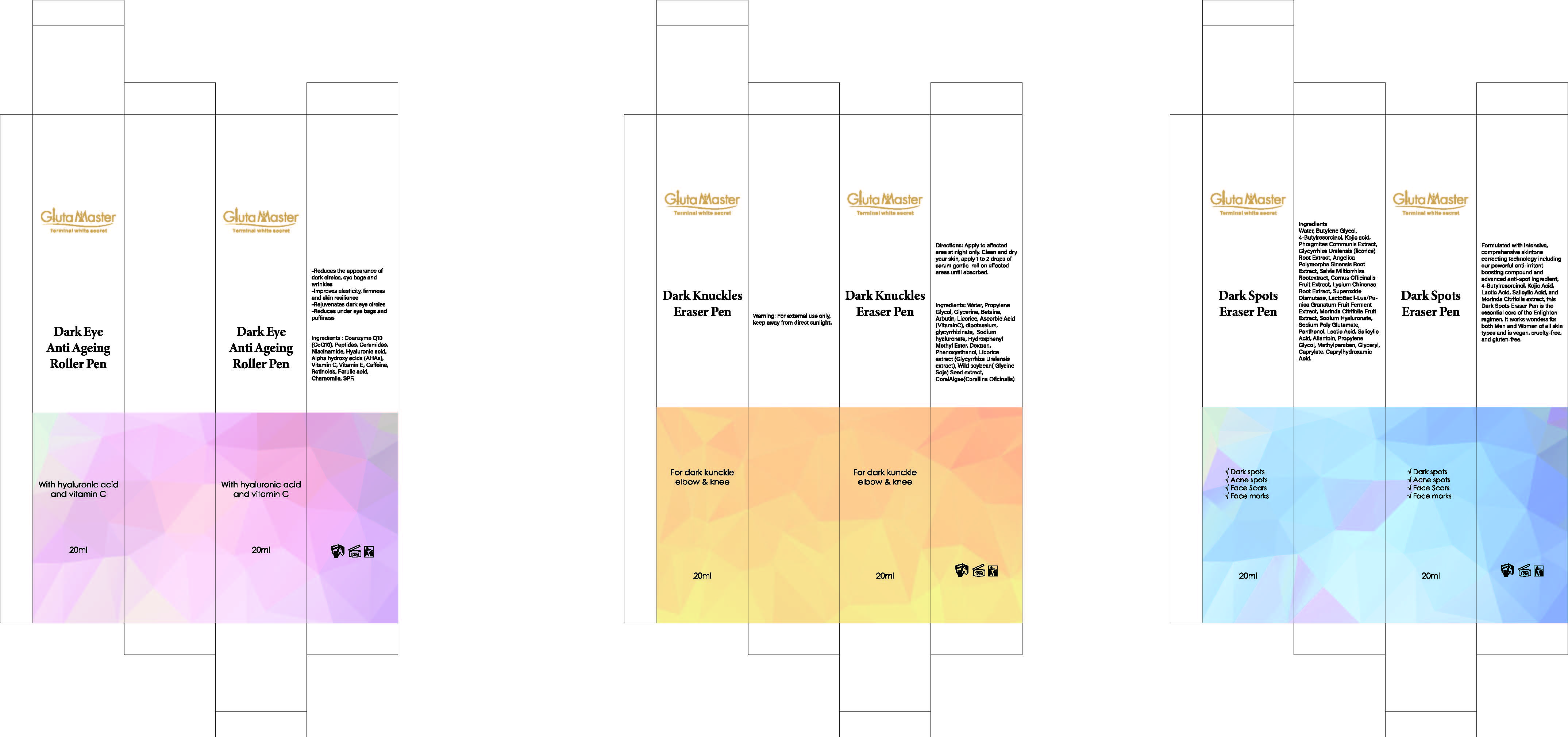 DRUG LABEL: dark knuckles eraser pen
NDC: 84423-086 | Form: LOTION, AUGMENTED
Manufacturer: Guangzhou Kadiya Biotechnology Co., Ltd.
Category: otc | Type: HUMAN OTC DRUG LABEL
Date: 20250801

ACTIVE INGREDIENTS: ARBUTIN 0.24 g/20 g; ASCORBIC ACID 0.4 g/20 g
INACTIVE INGREDIENTS: IRON DEXTRAN; PHENOXYETHANOL; PROPYLENE GLYCOL; LICORICE; WATER; GLYCYRRHIZIN; SODIUM HYALURONATE; SODIUM HYDROXIDE; GLYCERIN; SOYBEAN OIL; BETAINE; GLYCYRRHIZA GLABRA (LICORICE) ROOT POWDER; METHYLPARABEN

PURPOSE

For whitening, Moisturizing, Antioxidant

INACTIVE INGREDIENT

Water
PropyleneGlycol
Glycerine
Betaine
Licorice
dipotassium
glycyrrhizinate
Sodiumhyaluronate
HydroxphenyMethyl Ester
Dextran
Phenoxyethanol
Licoriceextract (Glycyrrhiza Uralensisextract)
Wild soybean(GlycineSoja) Seed extract

Warning.
1、For external use only, avoid contact with eyes when used
2、Keep out of reach of children

INACTIVE INGREDIENT

Apply to affected area at night only. Clean and dry your skin,

KEEP OUT OF REACH OF CHILDREN SECTION

ACTIVE INGREDIENT

Arbutin1.2%
Vitamin C2%

INDICATIONS AND USAGE

apply 1 to 2 drops of serum gentle roll on affected areas until absorbed.

DOSAGE AND ADMINISTRATION

apply 1 to 2 drops of serum gentle roll on affected areas until absorbed.

PACKAGE LABEL

Active Ingredients
Arbutin1.2%
Vitamin C2%
Uses：
For whitening, Moisturizing, Antioxidant
The storage method：
Store sealed in a cool place and out of sunlight
Warning.
1、For external use only, avoid contact with eyes when used
2、Keep out of reach of children
Water
PropyleneGlycol
Glycerine
Betaine
Licorice
dipotassium
glycyrrhizinate
Sodiumhyaluronate
HydroxphenyMethyl Ester
Dextran
Phenoxyethanol
Licoriceextract (Glycyrrhiza Uralensisextract)
Wild soybean(GlycineSoja) Seed extract